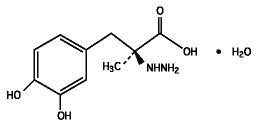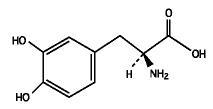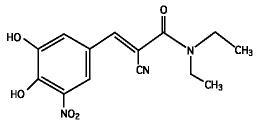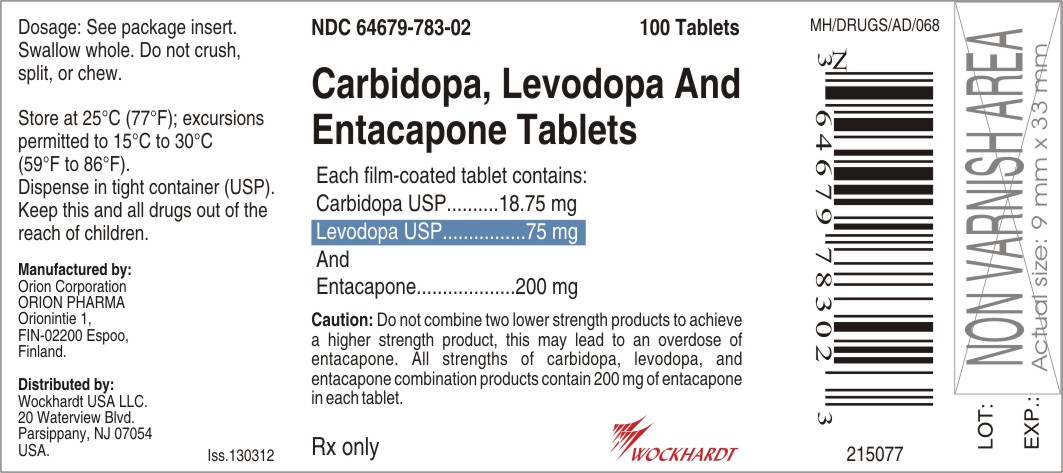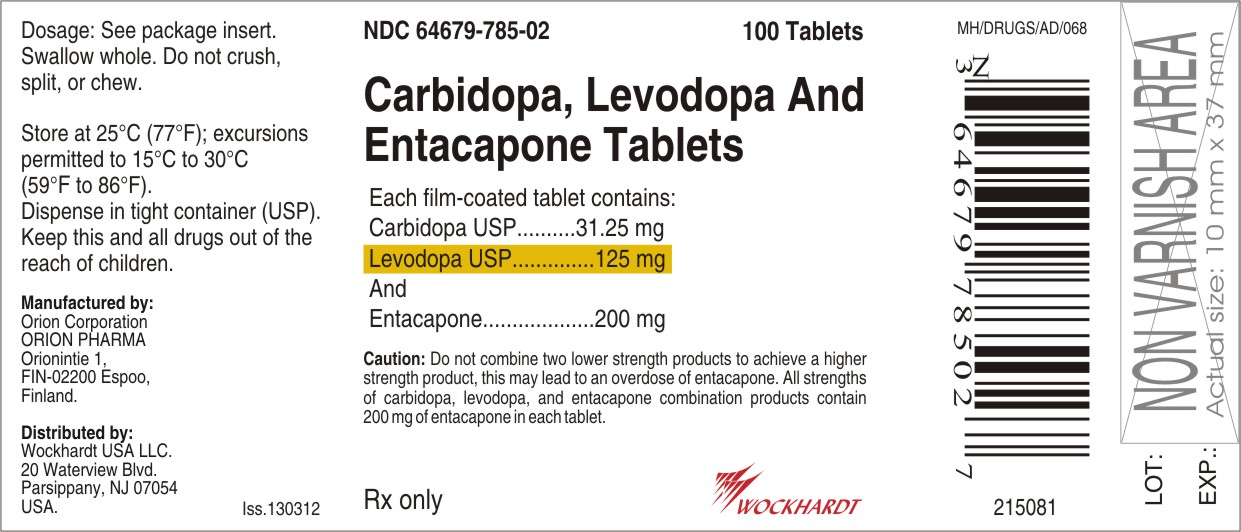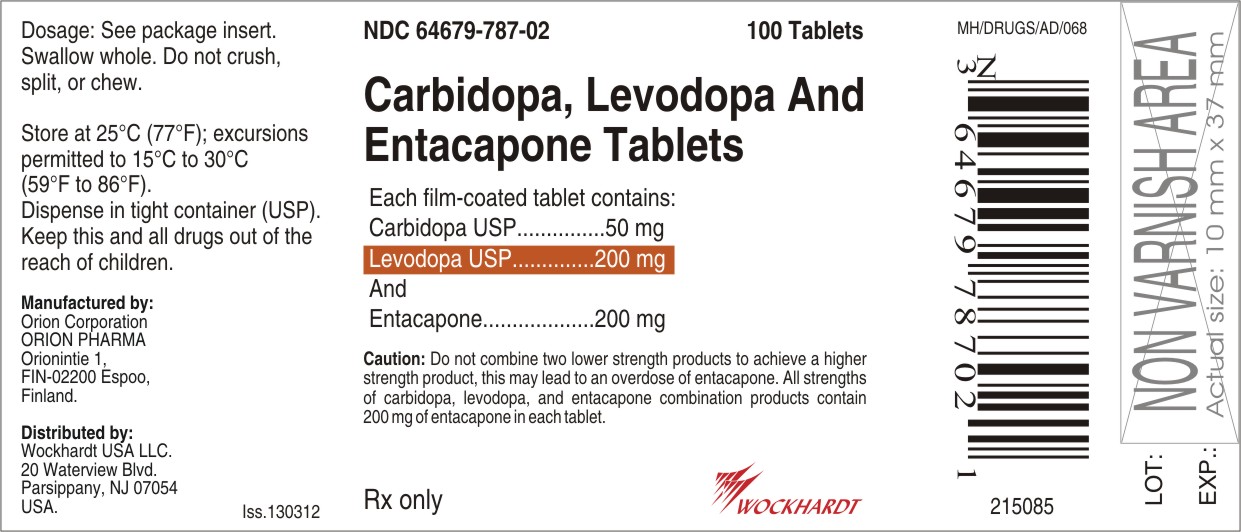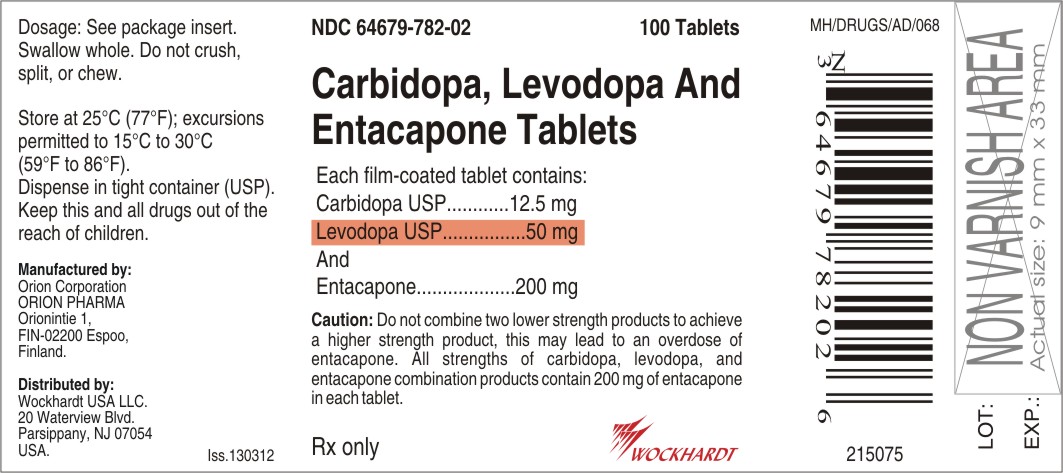 DRUG LABEL: carbidopa, levodopa and entacapone
NDC: 55648-782 | Form: TABLET, FILM COATED
Manufacturer: Wockhardt Limited
Category: prescription | Type: HUMAN PRESCRIPTION DRUG LABEL
Date: 20120528

ACTIVE INGREDIENTS: CARBIDOPA 12.5 mg/1 1; ENTACAPONE 200 mg/1 1; LEVODOPA 50 mg/1 1
INACTIVE INGREDIENTS: CROSCARMELLOSE SODIUM; FERRIC OXIDE RED; FERRIC OXIDE YELLOW; GLYCERIN; HYPROMELLOSES; MAGNESIUM STEARATE; MANNITOL; POLYSORBATE 80; POVIDONE; STARCH, CORN; SUCROSE; TITANIUM DIOXIDE

Carbidopa, Levodopa and Entacapone Tablets

Rx only

Prescribing Information

DESCRIPTION

Carbidopa, levodopa and entacapone tablet is a combination of carbidopa, levodopa and entacapone for the treatment of Parkinson’s disease.

Carbidopa, an inhibitor of aromatic amino acid decarboxylation, is a white, crystalline compound, slightly soluble in water, with a molecular weight of 244.3. It is designated chemically as (-)-L-(α-hydrazino-(α-methyl-β-(3,4-dihydroxybenzene) propanoic acid monohydrate. Its empirical formula is C10H14N2O4●H2O, and its structural formula is

Tablet content is expressed in terms of anhydrous carbidopa, which has a molecular weight of 226.3.

Levodopa, an aromatic amino acid, is a white, crystalline compound, slightly soluble in water, with a molecular weight of 197.2. It is designated chemically as (-)-L-α-amino-β-(3,4-dihydroxybenzene) propanoic acid. Its empirical formula is C9H11NO4, and its structural formula is

Entacapone, an inhibitor of catechol-O-methyltransferase (COMT), is a nitro-catechol-structured compound with a molecular weight of 305.3. The chemical name of entacapone is (E)-2-cyano-3-(3,4-dihydroxy-5-nitrophenyl)-N,N-diethyl-2-propenamide. Its empirical formula is C14H15N3O5 and its structural formula is

Carbidopa, levodopa and entacapone is supplied as tablets in six strengths:

Carbidopa, levodopa and entacapone tablet, containing 12.5 mg of carbidopa, 50 mg of levodopa and 200 mg of entacapone;

Carbidopa, levodopa and entacapone tablet, containing 18.75 mg of carbidopa, 75 mg of levodopa and 200 mg of entacapone;

Carbidopa, levodopa and entacapone tablet, containing 25 mg of carbidopa, 100 mg of levodopa and 200 mg of entacapone;

Carbidopa, levodopa and entacapone tablet, containing 31.25 mg of carbidopa, 125 mg of levodopa and 200 mg of entacapone;

Carbidopa, levodopa and entacapone tablet, containing 37.5 mg of carbidopa, 150 mg of levodopa and 200 mg of entacapone;

Carbidopa, levodopa and entacapone tablet, containing 50 mg of carbidopa, 200 mg of levodopa and 200 mg of entacapone.

The inactive ingredients of the carbidopa, levodopa and entacapone tablet are corn starch, croscarmellose sodium, glycerol 85%, hypromellose, magnesium stearate, mannitol, polysorbate 80, povidone, sucrose, red iron oxide, and titanium dioxide. Tablet containing 12.5 mg of carbidopa, 50 mg of levodopa and 200 mg of entacapone, tablet containing 25 mg of carbidopa, 100 mg of levodopa and 200 mg of entacapone, and tablet containing 37.5 mg of carbidopa, 150 mg of levodopa and 200 mg of entacapone also contain yellow iron oxide.

CLINICAL PHARMACOLOGY

Parkinson’s disease is a progressive, neurodegenerative disorder of the extrapyramidal nervous system affecting the mobility and control of the skeletal muscular system. Its characteristic features include resting tremor, rigidity, and bradykinetic movements.

Mechanism of Action

Levodopa

Current evidence indicates that symptoms of Parkinson’s disease are related to depletion of dopamine in the corpus striatum. Administration of dopamine is ineffective in the treatment of Parkinson’s disease apparently because it does not cross the blood-brain barrier. However, levodopa, the metabolic precursor of dopamine, does cross the blood-brain barrier, and presumably is converted to dopamine in the brain. This is thought to be the mechanism whereby levodopa relieves symptoms of Parkinson’s disease.

Carbidopa

When levodopa is administered orally it is rapidly decarboxylated to dopamine in extracerebral tissues so that only a small portion of a given dose is transported unchanged to the central nervous system. Carbidopa inhibits the decarboxylation of peripheral levodopa, making more levodopa available for transport to the brain. When coadministered with levodopa, carbidopa increases plasma levels of levodopa and reduces the amount of levodopa required to produce a given response by about 75%. Carbidopa prolongs the plasma halflife of levodopa from 50 minutes to 1.5 hours and decreases plasma and urinary dopamine and its major metabolite, homovanillic acid. The Tmax of levodopa, however, was unaffected by the coadministration.

Entacapone

Entacapone is a selective and reversible inhibitor of catechol-O-methyltransferase (COMT).

In mammals, COMT is distributed throughout various organs with the highest activities in the liver and kidney. COMT also occurs in neuronal tissues, especially in glial cells. COMT catalyzes the transfer of the methyl group of S-adenosyl-L-methionine to the phenolic group of substrates that contain a catechol structure. Physiological substrates of COMT include DOPA, catecholamines (dopamine, norepinephrine, and epinephrine) and their hydroxylated metabolites. The function of COMT is the elimination of biologically active catechols and some other hydroxylated metabolites. When decarboxylation of levodopa is prevented by carbidopa, COMT becomes the major metabolizing enzyme for levodopa, catalyzing its metabolism to 3-methoxy-4-hydroxy-L-phenylalanine (3-OMD).

When entacapone is given in conjunction with levodopa and carbidopa, plasma levels of levodopa are greater and more sustained than after administration of levodopa and carbidopa alone. It is believed that at a given frequency of levodopa administration, these more sustained plasma levels of levodopa result in more constant dopaminergic stimulation in the brain, leading to greater effects on the signs and symptoms of Parkinson’s disease. The higher levodopa levels may also lead to increased levodopa adverse effects, sometimes requiring a decrease in the dose of levodopa.

When 200 mg entacapone is coadministered with levodopa/carbidopa, it increases levodopa plasma exposure (AUC) by 35% to 40% and prolongs its elimination half-life in Parkinson’s disease patients from 1.3 hours to 2.4 hours. Plasma levels of the major COMT-mediated dopamine metabolite, 3-methoxy-4-hydroxy-L-phenylalanine (3-OMD), are also markedly decreased proportionally with increasing dose of entacapone.

In animals, while entacapone enters the CNS to a minimal extent, it has been shown to inhibit central COMT activity. In humans, entacapone inhibits the COMT enzyme in peripheral tissues. The effects of entacapone on central COMT activity in humans have not been studied.

Pharmacokinetics

The pharmacokinetics of carbidopa, levodopa and entacapone tablets have been studied in healthy subjects (age 45 years old to 75 years old). Overall, following administration of corresponding doses of levodopa, carbidopa and entacapone as carbidopa, levodopa and entacapone tablets or as carbidopa/levodopa product plus entacapone tablets, the mean plasma concentrations of levodopa, carbidopa, and entacapone are comparable.

Absorption/Distribution:

Both levodopa and entacapone are rapidly absorbed and eliminated, and their distribution volume is moderately small. Carbidopa is absorbed and eliminated slightly more slowly compared with levodopa and entacapone. There are substantial inter- and intra-individual variations in the absorption of levodopa, carbidopa and entacapone, particularly concerning its Cmax.

The food-effect on the carbidopa, levodopa and entacapone tablet has not been evaluated.

Levodopa

The pharmacokinetic properties of levodopa following the administration of single-dose carbidopa, levodopa and entacapone tablets are summarized in Table 1.

Table 1. Pharmacokinetic Characteristics of LevodopaWith Different Tablet Strengths of Carbidopa, Levodopa and Entacapone(mean ± SD)
 | AUC0-∞ | Cmax | Tmax
Tablet Strength | (nanogram·h/mL) | (nanogram/mL) | (h)
12.5 mg/50 mg/ 200 mg | 1,040 ± 314 | 470 ± 154 | 1.1 ± 0.5
25 mg/100 mg/ 200 mg | 2,910 ± 715 | 975 ± 247 | 1.4 ± 0.6
37.5 mg/150 mg/ 200 mg | 3,770 ± 1120 | 1,270 ± 329 | 1.5 ± 0.9
50 mg/200 mg/ 200 mg | 6,115 ± 1536 | 1,859 ± 455 | 1.76 ± 0.7

Since levodopa competes with certain amino acids for transport across the gut wall, the absorption of levodopa may be impaired in some patients on a high protein diet. Meals rich in large neutral amino acids may delay and reduce the absorption of levodopa (see PRECAUTIONS).

Levodopa is bound to plasma protein only to a minor extent (about 10% to 30%).

Carbidopa

Following administration of carbidopa, levodopa and entacapone tablet as a single dose to healthy male and female subjects, the peak concentration of carbidopa was reached within 2.5 hours to 3.4 hours on average. The mean Cmax ranged from about 40 nanogram/mL to 225 nanogram/mL and the mean AUC from 170 nanogram●h/mL to 1,200 nanogram●h/mL, with different carbidopa, levodopa and entacapone tablet strengths providing 12.5 mg, 25 mg, 37.5 mg or 50 mg of carbidopa.

Carbidopa is approximately 36% bound to plasma protein.

Entacapone

Following administration of carbidopa, levodopa and Entacapone tablets as a single dose to healthy male and female subjects, the peak concentration of entacapone in plasma was reached within 0.8 hours to 1.2 hours on average. The mean Cmax of entacapone was about 1,200 nanogram/mL to 1,500 nanogram/mL and the AUC 1,250 nanogram●h/mL to 1,750 nanogram●h/mL after administration of different carbidopa, levodopa and entacapone tablet strengths all providing 200 mg of entacapone.

The plasma protein binding of entacapone is 98% over the concentration range of 0.4 microgram/mL to 50 microgram/mL. Entacapone binds mainly to serum albumin.

Metabolism and Elimination:

Levodopa

The elimination half-life of levodopa, the active moiety of antiparkinsonian activity, was 1.7 hours (range 1.1 hours to 3.2 hours).

Levodopa is extensively metabolized to various metabolites. Two major pathways are decarboxylation by dopa decarboxylase (DDC) and O-methylation by catechol-O-methyltransferase (COMT).

Carbidopa

The elimination half-life of carbidopa was on average 1.6 hours to 2 hours (range 0.7 hours to 4.0 hours).

Carbidopa is metabolized to two main metabolites (α-methyl-3-methoxy-4-hydroxyphenylpropionic acid and α-methyl-3,4-dihydroxyphenylpropionic acid). These 2 metabolites are primarily eliminated in the urine unchanged or as glucuronide conjugates. Unchanged carbidopa accounts for 30% of the total urinary excretion.

Entacapone

The elimination half-life of entacapone was on average 0.8 hours to 1 hour (0.3 hours to 4.5 hours).

Entacapone is almost completely metabolized prior to excretion with only a very small amount (0.2% of dose) found unchanged in urine. The main metabolic pathway is isomerization to the cis-isomer, the only active metabolite. Entacapone and the cis-isomer are eliminated in the urine as glucuronide conjugates. The glucuronides account for 95% of all urinary metabolites (70% as parent and 25% as cis-isomer glucuronides). The glucuronide conjugate of the cis-isomer is inactive. After oral administration of a ^14C-labeled dose of entacapone, 10% of labeled parent and metabolite is excreted in urine and 90% in feces.

Due to short elimination half-lives, no true accumulation of levodopa or entacapone occurs when they are administered repeatedly.

Special Populations

Hepatic Impairment:

Carbidopa, levodopa and entacapone tablets

While there are no studies on the pharmacokinetics of carbidopa and levodopa in patients with hepatic impairment, a carbidopa, levodopa and entacapone tablets should be administered cautiously to patients with biliary obstruction or hepatic disease since biliary excretion appears to be the major route of excretion of entacapone and hepatic impairment had a significant effect on the pharmacokinetics of entacapone when 200 mg entacapone was administered alone.

Entacapone

Hepatic impairment had a significant effect on the pharmacokinetics of entacapone when 200 mg entacapone was administered alone. A single 200 mg dose of entacapone, without levodopa/dopa decarboxylase inhibitor coadministration, showed approximately two-fold higher AUC and Cmax values in patients with a history of alcoholism and hepatic impairment (n=10) compared to normal subjects (n=10). All patients had biopsy-proven liver cirrhosis caused by alcohol. According to Child-Pugh grading 7 patients with liver disease had mild hepatic impairment and 3 patients had moderate hepatic impairment. As only about 10% of the entacapone dose is excreted in urine, as parent compound and conjugated glucuronide, biliary excretion appears to be the major route of excretion of this drug. Consequently, carbidopa, levodopa and entacapone tablets should be administered with care to patients with biliary obstruction or hepatic disease.

Renal Impairment:

Carbidopa, levodopa and entacapone tablets

Carbidopa, levodopa and entacapone tablets should be administered cautiously to patients with severe renal disease. There are no studies on the pharmacokinetics of levodopa and carbidopa in patients with renal impairment.

Entacapone

No important effects of renal function on the pharmacokinetics of entacapone were found. The pharmacokinetics of entacapone have been investigated after a single 200 mg entacapone dose, without levodopa/dopa decarboxylase inhibitor coadministration, in a specific renal impairment study. There were three groups: normal subjects (n=7; creatinine clearance greater than 1.12 mL/sec/1.73 m^2), moderate impairment (n=10; creatinine clearance ranging from 0.60 mL/sec/1.73 m^2 to 0.89 mL/sec/1.73 m^2), and severe impairment (n=7; creatinine clearance ranging from 0.20 mL/sec/1.73 m^2 to 0.44 mL/sec/1.73 m^2).

Concurrent Diseases:

Carbidopa, levodopa and entacapone tablets should be administered cautiously to patients with biliary obstruction, hepatic disease, severe cardiovascular or pulmonary disease, bronchial asthma, renal, or endocrine disease.

Elderly:

Carbidopa, levodopa and entacapone tablets have not been studied in Parkinson’s disease patients or in healthy volunteers older than 75 years old. In the pharmacokinetics studies conducted in healthy volunteers following single dose of carbidopa/levodopa/entacapone (as carbidopa, levodopa and entacapone tablets or as separate carbidopa/levodopa and entacapone tablets):

Levodopa

The AUC of levodopa is significantly (on average 10% to 20%) higher in elderly (60 years to 75 years) than younger subjects (45 years to 60 years). There is no significant difference in the Cmax of levodopa between younger (45 years to 60 years) and elderly subjects (60 years to 75 years).

Carbidopa

There is no significant difference in the Cmax and AUC of carbidopa, between younger (45 years to 60 years) and elderly subjects (60 years to 75 years).

Entacapone

The AUC of entacapone is significantly (on average, 15%) higher in elderly (60 years to 75 years) than younger subjects (45 years to 60 years). There is no significant difference in the Cmax of entacapone between younger (45 years to 60 years) and elderly subjects (60 years to 75 years).

Gender:

The bioavailability of levodopa is significantly higher in females when given with or without carbidopa and/or entacapone. Following a single dose of carbidopa, levodopa and entacapone together, either as carbidopa, levodopa and entacapone tablets or as separate carbidopa/levodopa and entacapone tablets in healthy volunteers (age range 45 years to 74 years):

Levodopa

The plasma exposure (AUC and Cmax) of levodopa is significantly higher in females than males (on average, 40% for AUC and 30% for Cmax). These differences are primarily explained by body weight. Other published literature showed significant gender effect (higher concentrations in females) even after correction for body weight.

Carbidopa

There is no gender difference in the pharmacokinetics of carbidopa.

Entacapone

There is no gender difference in the pharmacokinetics of entacapone.

Drug Interactions

See PRECAUTIONS, Drug Interactions.

Clinical Studies

Each carbidopa, levodopa and entacapone tablet, provided in six single-dose strengths, contains carbidopa and levodopa in ratio 1:4 and a 200 mg dose of entacapone. Four carbidopa, levodopa and entacapone tablet strengths 12.5 mg/50 mg/200 mg, 25 mg/100 mg/200 mg, 37.5 mg/150 mg/200 mg and 50 mg/200 mg/200 mg have been shown to be bioequivalent to the corresponding doses of standard-release carbidopa/levodopa 25 mg/100 mg tablets and entacapone 200 mg tablets.

The effectiveness of entacapone as an adjunct to levodopa in the treatment of Parkinson’s disease was established in three 24-week multicenter, randomized, double-blind placebo-controlled trials in patients with Parkinson’s disease. In two of these trials, the patients’ disease was "fluctuating", i.e., was characterized by documented periods of "On" (periods of relatively good functioning) and "Off" (periods of relatively poor functioning), despite optimum levodopa therapy. There was also a withdrawal period following 6 months of treatment. In the third trial patients were not required to have been experiencing fluctuations. Prior to the controlled part of these trials, patients were stabilized on levodopa for 2 weeks to 4 weeks.

There is limited experience of using entacapone in patients who do not experience fluctuations.

In the first two studies to be described, patients were randomized to receive placebo or entacapone 200 mg administered concomitantly with each dose of carbidopa-levodopa (up to 10 times daily, but averaging 4 doses to 6 doses per day). The formal double-blind portion of both trials was 6 months long. Patients recorded the time spent in the "On" and "Off" states in home diaries periodically throughout the duration of the trial. In one study, conducted in the Nordic countries, the primary outcome measure was the total mean time spent in the "On" state during an 18-hour diary recorded day (6 a.m. to midnight). In the other study, the primary outcome measure was the proportion of awake time spent over 24 hours in the "On" state.

In addition to the primary outcome measure, the amount of time spent in the "Off" state was evaluated, and patients were also evaluated by subparts of the Unified Parkinson’s Disease Rating Scale (UPDRS), a frequently used multi-item rating scale intended to assess mentation (Part I), activities of daily living (Part II), motor function (Part III), complications of therapy (Part IV), and disease staging (Part V and VI); an investigator’s and patient’s global assessment of clinical condition, a 7-point subjective scale designed to assess global functioning in Parkinson’s disease; and the change in daily carbidopa-levodopa dose.

In one of the studies, 171 patients were randomized in 16 centers in Finland, Norway, Sweden, and Denmark (Nordic study), all of whom received concomitant levodopa plus dopa-decarboxylase inhibitor (either carbidopa-levodopa or benserazide-levodopa). In the second trial, 205 patients were randomized in 17 centers in North America (US and Canada); all patients received concomitant carbidopa-levodopa.

The following tables display the results of these two trials:

Table 2. Nordic Study
Primary Measure from Home Diary (from an 18-hour Diary Day)
 | Baseline | Change from Baseline at Month 6* | p-value vs. placebo
Hours of Awake Time “On”
Placebo | 9.2 | +0.1 | -
Entacapone | 9.3 | +1.5 | <0.001
Duration of “On” Time After First AM Dose (Hrs)
Placebo | 2.2 | 0.0 | -
Entacapone | 2.1 | +0.2 | <0.05
Secondary Measures from Home Diary (from an 18-hour Diary Day)
Hours of Awake Time “Off”
Placebo | 5.3 | 0.0 | -
Entacapone | 5.5 | -1.3 | <0.001
Proportion of Awake Time “On” *** (%)
Placebo | 63.8 | +0.6 | -
Entacapone | 62.7 | +9.3 | <0.001
Levodopa Total Daily Dose (mg)
Placebo | 705 | +14 | -
Entacapone | 701 | -87 | <0.001
Frequency of Levodopa Daily Intakes
Placebo | 6.1 | +0.1 | -
Entacapone | 6.2 | -0.4 | <0.001
Other Secondary Measures
 | Baseline | Change from Baseline at Month 6 | p-value vs. placebo
Investigator’s Global (overall) % Improved**
Placebo | - | 28 | -
Entacapone | - | 56 | <0.01
Patient’s Global (overall) % Improved**
Placebo | - | 22 | -
Entacapone | - | 39 | N.S. ‡
UPDRS Total
Placebo | 37.4 | -1.1 | -
Entacapone | 38.5 | -4.8 | <0.01
UPDRS Motor
Placebo | 24.6 | -0.7 | -
Entacapone | 25.5 | -3.3 | <0.05
UPDRS ADL
Placebo | 11.0 | -0.4 | -
Entacapone | 11.2 | -1.8 | <0.05
* Mean; the month 6 values represent the average of weeks 8, 16, and 24, by
protocol-defined outcome measure.
** At least one category change at endpoint.
*** Not an endpoint for this study but primary endpoint in the North American Study.
‡ Not significant.

Table 3. North American Study
Primary Measure from Home Diary (for a 24-hour Diary Day)
 | Baseline | Change from Baseline at Month 6* | p-value vs. placebo
Percent of Awake Time “On”
Placebo | 60.8 | +2.0 | -
Entacapone | 60.0 | +6.7 | <0.05
Secondary Measures from Home Diary (for a 24-hour Diary Day)
Hours of Awake Time “Off”
Placebo | 6.6 | -0.3 | -
Entacapone | 6.8 | -1.2 | <0.01
Hours of Awake Time “On”
Placebo | 10.3 | +0.4 | -
Entacapone | 10.2 | +1.0 | N.S. ‡
Levodopa Total Daily Dose (mg)
Placebo | 758 | +19 | -
Entacapone | 804 | -93 | <0.001
Frequency of Levodopa Daily Intakes
Placebo | 6.0 | +0.2 | -
Entacapone | 6.2 | 0.0 | N.S. ‡
Other Secondary Measures
 | Baseline | Change from Baseline at Month 6 | p-value vs. placebo
Investigator’s Global (overall) % Improved**
Placebo | - | 21 | -
Entacapone | - | 34 | <0.05
Patient’s Global (overall) % Improved**
Placebo | - | 20 | -
Entacapone | - | 31 | <0.05
UPDRS Total***
Placebo | 35.6 | +2.8 | -
Entacapone | 35.1 | -0.6 | <0.05
UPDRS Motor***
Placebo | 22.6 | +1.2 | -
Entacapone | 22.0 | -0.9 | <0.05
UPDRS ADL***
Placebo | 11.7 | +1.1 | -
Entacapone | 11.9 | 0.0 | <0.05
* Mean; the month 6 values represent the average of weeks 8, 16, and 24, by
protocol-defined outcome measure.
** At least one category change at endpoint.
*** Score change at endpoint similarly to the Nordic Study.
‡Not significant.

Effects on "On" time did not differ by age, sex, weight, disease severity at baseline, levodopa dose and concurrent treatment with dopamine agonists or selegiline.

Withdrawal of entacapone:

In the North American study, abrupt withdrawal of entacapone, without alteration of the dose of carbidopa-levodopa, resulted in a significant worsening of fluctuations, compared to placebo. In some cases, symptoms were slightly worse than at baseline, but returned to approximately baseline severity within two weeks following levodopa dose increase on average by 80 mg. In the Nordic study, similarly, a significant worsening of parkinsonian symptoms was observed after entacapone withdrawal, as assessed two weeks after drug withdrawal. At this phase, the symptoms were approximately at baseline severity following levodopa dose increase by about 50 mg.

In the third placebo-controlled trial, a total of 301 patients were randomized in 32 centers in Germany and Austria. In this trial, as in the other two trials, entacapone 200 mg was administered with each dose of levodopa/dopa decarboxylase inhibitor (up to 10 times daily) and UPDRS Parts II and III and total daily "On" time were the primary measures of effectiveness. The following results were seen for the primary measures, as well as for some secondary measures:

Table 4. German-Austrian Study
Primary Measures
 | Baseline | Change from Baseline at Month 6 | p-value vs. placebo (LOCF)
UPDRS ADL*
Placebo | 12.0 | + 0.5 | -
Entacapone | 12.4 | - 0.4 | <0.05
UPDRS Motor*
Placebo | 24.1 | + 0.1 | -
Entacapone | 24.9 | - 2.5 | <0.05
Hours of Awake Time “On” (Home Diary) **
Placebo | 10.1 | + 0.5 | -
Entacapone | 10.2 | + 1.1 | N.S. ‡
Secondary Measures
 | Baseline | Change from Baseline at Month 6 | p-value vs. placebo
UPDRS Total*
Placebo | 37.7 | + 0.6 | -
Entacapone | 39.0 | - 3.4 | <0.05
Percent of Awake Time “On” (Home Diary)**
Placebo | 59.8 | + 3.5 | -
Entacapone | 62.0 | + 6.5 | N.S. ‡
Hours of Awake Time “Off” (Home Diary)**
Placebo | 6.8 | - 0.6 | -
Entacapone | 6.3 | - 1.2 | 0.07
Levodopa Total Daily Dose (mg)*
Placebo | 572 | + 4 | -
Entacapone | 566 | - 35 | N.S. ‡
Frequency of Levodopa Daily Intake*
Placebo | 5.6 | + 0.2 | -
Entacapone | 5.4 | 0.0 | <0.01
Global (overall) % Improved***
Placebo | - | 34 | -
Entacapone | - | 38 | N.S. ‡
* Total population; score change at endpoint.
** Fluctuating population, with 5 doses to 10 doses; score change at endpoint.
*** Total population; at least one category change at endpoint.
‡Not significant.

INDICATIONS AND USAGE

1. To substitute (with equivalent strength of each of the three components) for immediate-release carbidopa/levodopa and entacapone previously administered as individual products.
2. To replace immediate-release carbidopa/levodopa therapy (without entacapone) when patients experience the signs and symptoms of end-of-dose "wearing-off" (only for patients taking a total daily dose of levodopa of 600 mg or less and not experiencing dyskinesias, see DOSAGE AND ADMINISTRATION).

CONTRAINDICATIONS

Carbidopa, levodopa and entacapone tablets are contraindicated in patients who have demonstrated hypersensitivity to any component (carbidopa, levodopa, or entacapone) of the drug or its excipients.

Monoamine oxidase (MAO) and COMT are the two major enzyme systems involved in the metabolism of catecholamines. It is theoretically possible, therefore, that the combination of entacapone and a non-selective MAO inhibitor (e.g., phenelzine and tranylcypromine) would result in inhibition of the majority of the pathways responsible for normal catecholamine metabolism. As with carbidopa-levodopa, nonselective monoamine oxidase (MAO) inhibitors are contraindicated for use with carbidopa, levodopa and entacapone tablets. These inhibitors must be discontinued at least two weeks prior to initiating therapy with carbidopa, levodopa and entacapone tablets. Carbidopa, levodopa and entacapone tablets may be administered concomitantly with the manufacturer’s recommended dose of MAO inhibitors with selectivity for MAO type B (e.g., selegiline HCl). (See PRECAUTIONS, Drug Interactions.)

Carbidopa, levodopa and entacapone tablets are contraindicated in patients with narrow-angle glaucoma.

Because levodopa may activate malignant melanoma, carbidopa, levodopa and entacapone tablets should not be used in patients with suspicious, undiagnosed skin lesions or a history of melanoma.

WARNINGS

The addition of carbidopa to levodopa reduces the peripheral effects (nausea, vomiting) due to decarboxylation of levodopa; however, carbidopa does not decrease the adverse reactions due to the central effects of levodopa. Because carbidopa as well as entacapone permits more levodopa to reach the brain and more dopamine to be formed, certain adverse CNS effects, e.g., dyskinesia (involuntary movements) may occur at lower dosages and sooner with levodopa preparations containing carbidopa and entacapone than with levodopa alone.

The occurrence of dyskinesias may require dosage reduction (see PRECAUTIONS, Dyskinesia).

Carbidopa, levodopa and entacapone tablets may cause mental disturbances. These reactions are thought to be due to increased brain dopamine following administration of levodopa. All patients should be observed carefully for the development of depression with concomitant suicidal tendencies. Patients with past or current psychoses should be treated with caution.

Carbidopa, levodopa and entacapone tablets should be administered cautiously to patients with severe cardiovascular or pulmonary disease, bronchial asthma, renal, hepatic or endocrine disease.

As with levodopa, care should be exercised in administering combination of carbidopa, levodopa and entacapone to patients with a history of myocardial infarction who have residual atrial, nodal, or ventricular arrhythmias. In such patients, cardiac function should be monitored carefully during the period of initial dosage adjustment, in a facility with provisions for intensive cardiac care.

As with levodopa, treatment with combination of carbidopa, levodopa and entacapone may increase the possibility of upper gastrointestinal hemorrhage in patients with a history of peptic ulcer.

Neuroleptic Malignant Syndrome (NMS)

Sporadic cases of a symptom complex resembling NMS have been reported in association with dose reductions or withdrawal of therapy with carbidopa-levodopa. Therefore, patients should be observed carefully when the dosage of a carbidopa, levodopa and entacapone tablets is reduced abruptly or discontinued, especially if the patient is receiving neuroleptics. NMS is an uncommon but life-threatening syndrome characterized by fever or hyperthermia. Neurological findings, including muscle rigidity, involuntary movements, altered consciousness, mental status changes; other disturbances, such as autonomic dysfunction, tachycardia, tachypnea, sweating, hyper- or hypotension; laboratory findings, such as creatine phosphokinase elevation, leukocytosis, myoglobinuria, and increased serum myoglobin have been reported.

The early diagnosis of this condition is important for the appropriate management of these patients. Considering NMS as a possible diagnosis and ruling out other acute illnesses (e.g., pneumonia, systemic infection, etc.) is essential. This may be especially complex if the clinical presentation includes both serious medical illness and untreated or inadequately treated extrapyramidal signs and symptoms (EPS). Other important considerations in the differential diagnosis include central anticholinergic toxicity, heat stroke, drug fever, and primary central nervous system (CNS) pathology.

The management of NMS should include: 1) intensive symptomatic treatment and medical monitoring and 2) treatment of any concomitant serious medical problems for which specific treatments are available. Dopamine agonists, such as bromocriptine, and muscle relaxants, such as dantrolene, are often used in the treatment of NMS, however, their effectiveness has not been demonstrated in controlled studies.

Drugs Metabolized By Catechol-O-Methyltransferase (COMT)

When a single 400 mg dose of entacapone was given together with intravenous isoprenaline (isoproterenol) and epinephrine without coadministered levodopa/dopa decarboxylase inhibitor, the overall mean maximal changes in heart rate during infusion were about 50% and 80% higher than with placebo, for isoprenaline and epinephrine, respectively.

Therefore, drugs known to be metabolized by COMT, such as isoproterenol, epinephrine, norepinephrine, dopamine, dobutamine, alpha-methyldopa, apomorphine, isoetherine, and bitolterol should be administered with caution in patients receiving entacapone regardless of the route of administration (including inhalation), as their interaction may result in increased heart rates, possibly arrhythmias, and excessive changes in blood pressure.

Ventricular tachycardia was noted in one 32-year-old healthy male volunteer in an interaction study after epinephrine infusion and oral entacapone administration. Treatment with propranolol was required. A causal relationship to entacapone administration appears probable but cannot be attributed with certainty.

PRECAUTIONS

General

As with levodopa, periodic evaluations of hepatic, hematopoietic, cardiovascular, and renal function are recommended during extended therapy.

Patients with chronic wide-angle glaucoma may be treated cautiously with carbidopa, levodopa and entacapone tablets provided the intraocular pressure is well controlled and the patient is monitored carefully for changes in intraocular pressure during therapy.

Hypotension/Syncope

In the large controlled trials of entacapone, approximately 1.2% and 0.8% of 200 mg entacapone and placebo patients treated also with levodopa/dopa decarboxylase inhibitor, respectively, reported at least one episode of syncope. Reports of syncope were generally more frequent in patients in both treatment groups who had an episode of documented hypotension (although the episodes of syncope, obtained by history, were themselves not documented with vital sign measurement).

Diarrhea and Colitis

In clinical trials of entacapone, diarrhea developed in 60 of 603 (10.0%) and 16 of 400 (4.0%) of patients treated with 200 mg of entacapone or placebo in combination with levodopa/dopa decarboxylase inhibitor, respectively. In patients treated with entacapone, diarrhea was generally mild to moderate in severity (8.6%) but was regarded as severe in 1.3%. Diarrhea resulted in withdrawal in 10 of 603 (1.7%) patients, 7 (1.2%) with mild and moderate diarrhea and 3 (0.5%) with severe diarrhea. Diarrhea generally resolved after discontinuation of entacapone. Two patients with diarrhea were hospitalized. Typically, diarrhea presents within 4 weeks to 12 weeks after entacapone is started, but it may appear as early as the first week and as late as many months after the initiation of treatment. Diarrhea may be associated with weight loss, dehydration, and hypokalemia.

Postmarketing experience has shown that diarrhea may be a sign of drug-induced microscopic colitis, primarily lymphocytic colitis. In these cases diarrhea has usually been moderate to severe, watery and non-bloody, at times associated with dehydration, abdominal pain,weight loss, and hypokalemia. In the majority of cases, diarrhea and other colitis-related symptoms resolved or significantly improved when entacapone treatment was stopped. In some patients with biopsy confirmed colitis, diarrhea had resolved or significantly improved after discontinuation of entacapone but recurred after retreatment with entacapone.

If prolonged diarrhea is suspected to be related to carbidopa, levodopa and entacapone tablets, the drug should be discontinued and appropriate medical therapy considered. If the cause of prolonged diarrhea remains unclear or continues after stopping entacapone, then further diagnostic investigations including colonoscopy and biopsies should be considered.

Hallucinations

Dopaminergic therapy in Parkinson’s disease patients has been associated with hallucinations. In clinical trials of entacapone, hallucinations developed in approximately 4.0% of patients treated with 200 mg entacapone or placebo in combination with levodopa/dopa decarboxylase inhibitor. Hallucinations led to drug discontinuation and premature withdrawal from clinical trials in 0.8% and 0% of patients treated with 200 mg entacapone and placebo, respectively. Hallucinations led to hospitalization in 1.0% and 0.3% of patients in the 200 mg entacapone and placebo groups, respectively.

Dyskinesia

Entacapone may potentiate the dopaminergic side effects of levodopa and may therefore cause and/or exacerbate preexisting dyskinesia. Although decreasing the dose of levodopa may ameliorate this side effect, many patients in controlled trials continued to experience frequent dyskinesias despite a reduction in their dose of levodopa. The rates of withdrawal for dyskinesia were 1.5% and 0.8% for 200 mg entacapone and placebo, respectively.

Other Events Reported With Dopaminergic Therapy

The events listed below are rare events known to be associated with the use of drugs that increase dopaminergic activity, although they are most often associated with the use of direct dopamine agonists.

Rhabdomyolysis: Cases of severe rhabdomyolysis have been reported with entacapone when used in combination with levodopa. The complicated nature of these cases makes it impossible to determine what role, if any, entacapone played in their pathogenesis. Severe prolonged motor activity including dyskinesia may account for rhabdomyolysis. One case, however, included fever and alteration of consciousness. It is therefore possible that the rhabdomyolysis may be a result of the syndrome described in Hyperpyrexia and Confusion (see PRECAUTIONS, Other Events Reported With Dopaminergic Therapy).

Hyperpyrexia and Confusion: Cases of a symptom complex resembling the neuroleptic malignant syndrome characterized by elevated temperature, muscular rigidity, altered consciousness, and elevated CPK have been reported in association with the rapid dose reduction or withdrawal of other dopaminergic drugs. No cases have been reported following the abrupt withdrawal or dose reduction of entacapone treatment during clinical studies.

Prescribers should exercise caution when discontinuing carbidopa, levodopa and entacapone combination treatment. When considered necessary, withdrawal should proceed slowly. If a decision is made to discontinue treatment with carbidopa, levodopa and entacapone tablets, recommendations include monitoring the patient closely and adjusting other dopaminergic treatments as needed. This syndrome should be considered in the differential diagnosis for any patient who develops a high fever or severe rigidity. Tapering entacapone has not been systematically evaluated.

Fibrotic Complications: Cases of retroperitoneal fibrosis, pulmonary infiltrates, pleural effusion, and pleural thickening have been reported in some patients treated with ergot derived dopaminergic agents. These complications may resolve when the drug is discontinued, but complete resolution does not always occur. Although these adverse events are believed to be related to the ergoline structure of these compounds, whether other, nonergot derived drugs (e.g., entacapone, levodopa) that increase dopaminergic activity can cause them is unknown. It should be noted that the expected incidence of fibrotic complications is so low that even if entacapone caused these complications at rates similar to those attributable to other dopaminergic therapies, it is unlikely that it would have been detected in a cohort of the size exposed to entacapone. Four cases of pulmonary fibrosis were reported during clinical development of entacapone; three of these patients were also treated with pergolide and one with bromocriptine. The duration of treatment with entacapone ranged from 7 months to 17 months.

Melanoma: Epidemiological studies have shown that patients with Parkinson’s disease have a higher risk (2- to approximately 6-fold higher) of developing melanoma than the general population. Whether the increased risk observed was due to Parkinson’s disease or other factors, such as drugs used to treat Parkinson’s disease, is unclear.

For the reasons stated above, patients and providers are advised to monitor for melanomas frequently and on a regular basis when using carbidopa, levodopa and entacapone tablets for any indication. Ideally, periodic skin examination should be performed by appropriately qualified individuals (e.g., dermatologists).

Renal Toxicity

In a one-year toxicity study, entacapone (plasma exposure 20 times that in humans receiving the maximum recommended daily dose of 1,600 mg) caused an increased incidence of nephrotoxicity in male rats that was characterized by regenerative tubules, thickening of basement membranes, infiltration of mononuclear cells and tubular protein casts. These effects were not associated with changes in clinical chemistry parameters, and there is no established method for monitoring for the possible occurrence of these lesions in humans. Although this toxicity could represent a species-specific effect, there is not yet evidence that this is so.

Hepatic Impairment

Patients with hepatic impairment should be treated with caution. The AUC and Cmax of entacapone approximately doubled in patients with documented liver disease compared to controls. (See CLINICAL PHARMACOLOGY, Pharmacokinetics, and DOSAGE AND ADMINISTRATION).

Biliary Obstruction

Caution should be exercised when administering carbidopa, levodopa and entacapone tablets to patients with biliary obstruction, as entacapone is excreted mostly via the bile.

Information for Patients

The patient should be instructed to take carbidopa, levodopa and entacapone tablets only as prescribed. The patient should be informed that the carbidopa, levodopa and entacapone tablet is a standard-release formulation of carbidopa-levodopa combined with entacapone that is designed to begin release of ingredients within 30 minutes after ingestion. It is important that carbidopa, levodopa and entacapone tablets be taken at regular intervals according to the schedule outlined by the physician. The patient should be cautioned not to change the prescribed dosage regimen and not to add any additional antiparkinsonian medications, including other carbidopa-levodopa preparations, without first consulting the physician.

Patients should be advised that sometimes a "wearing-off" effect may occur at the end of the dosing interval. The physician should be notified for possible treatment adjustments if such response poses a problem to patient’s everyday life.

Patients should be advised that occasionally, dark color (red, brown, or black) may appear in saliva, urine, or sweat after ingestion of carbidopa, levodopa and entacapone tablets. Although the color appears to be clinically insignificant, garments may become discolored.

The patient should be advised that a change in diet to foods that are high in protein may delay the absorption of levodopa and may reduce the amount taken up in the circulation. Excessive acidity also delays stomach emptying, thus delaying the absorption of levodopa. Iron salts (such as in multi-vitamin tablets) may also reduce the amount of levodopa available to the body. The above factors may reduce the clinical effectiveness of the levodopa, carbidopa-levodopa and carbidopa, levodopa and entacapone tablets therapy.

NOTE: The suggested advice to patients being treated with carbidopa, levodopa and entacapone tablets is intended to aid in the safe and effective use of this medication. It is not a disclosure of all possible adverse or intended effects.

Patients should be informed that hallucinations can occur.

Patients should be advised that they may develop postural (orthostatic) hypotension with or without symptoms such as dizziness, nausea, syncope, and sweating. Hypotension may occur more frequently during initial therapy or when total daily levodopa dosage is increased. Accordingly, patients should be cautioned against rising rapidly after sitting or lying down, especially if they have been doing so for prolonged periods, and especially at the initiation of treatment with carbidopa, levodopa and entacapone tablets.

Patients should be advised that they should neither drive a car nor operate other complex machinery until they have gained sufficient experience on carbidopa, levodopa and entacapone tablets to gauge whether or not it affects their mental and/or motor performance adversely. Because of the possible additive sedative effects, caution should be used when patients are taking other CNS depressants in combination with carbidopa, levodopa and entacapone tablets.

Patients should be informed that nausea may occur, especially at the initiation of treatment with carbidopa, levodopa and entacapone tablets.

Patients should be informed that diarrhea may occur with carbidopa, levodopa and entacapone tablets and it may have a delayed onset. Sometimes prolonged diarrhea may be caused by colitis (inflammation of the large intestine). Patients with diarrhea should drink fluids to maintain adequate hydration and monitor for weight loss. If diarrhea associated with carbidopa, levodopa and entacapone tablets is prolonged, discontinuing the drug is expected to lead to resolution, if diarrhea continues after stopping carbidopa, levodopa and entacapone tablets, further diagnostic investigations may be needed.

Patients should be advised of the possibility of an increase in dyskinesia.

Carbidopa-levodopa combination and entacapone are known to affect embryo-fetal development in the rabbit and in the rat, respectively. Accordingly, patients should be advised to notify their physicians if they become pregnant or intend to become pregnant during therapy (see PRECAUTIONS, Pregnancy).

Carbidopa and entacapone are known to be excreted into maternal milk in rats. Because of the possibility that carbidopa, levodopa and entacapone may be excreted into human maternal milk, patients should be advised to notify their physicians if they intend to breast-feed or are breast-feeding an infant.

There have been reports of patients experiencing intense urges to gamble, increased sexual urges, and other intense urges and the inability to control these urges while taking one or more of the medications that increase central dopaminergic tone, that are generally used for the treatment of Parkinson’s disease, including carbidopa, levodopa and entacapone tablets. Although it is not proven that the medications caused these events, these urges were reported to have stopped in some cases when the dose was reduced or the medication was stopped. Prescribers should ask patients about the development of new or increased gambling urges, sexual urges or other urges while being treated with carbidopa, levodopa and entacapone tablets. Patients should inform their physician if they experience new or increased gambling urges, increased sexual urges or other intense urges while taking carbidopa, levodopa and entacapone tablets. Physicians should consider dose reduction or stopping the medication if a patient develops such urges while taking carbidopa, levodopa and entacapone tablets.

Laboratory Tests

Abnormalities in laboratory tests may include elevations of liver function tests such as alkaline phosphatase, SGOT (AST), SGPT (ALT), lactic dehydrogenase, and bilirubin. Abnormalities in blood urea nitrogen and positive Coombs’ test have also been reported. Commonly, levels of blood urea nitrogen, creatinine, and uric acid are lower during administration of a combination of carbidopa, levodopa and entacapone than with levodopa.

Carbidopa, levodopa and entacapone tablets may cause a false-positive reaction for urinary ketone bodies when a test tape is used for determination of ketonuria. This reaction will not be altered by boiling the urine specimen. False-negative tests may result with the use of glucose-oxidase methods of testing for glucosuria.

Cases of falsely diagnosed pheochromocytoma in patients on carbidopa-levodopa therapy have been reported very rarely. Caution should be exercised when interpreting the plasma and urine levels of catecholamines and their metabolites in patients on carbidopa-levodopa therapy.

Entacapone is a chelator of iron. The impact of entacapone on the body’s iron stores is unknown; however, a tendency towards decreasing serum iron concentrations was noted in clinical trials. In a controlled clinical study serum ferritin levels (as marker of iron deficiency and subclinical anemia) were not changed with entacapone compared to placebo after one year of treatment and there was no difference in rates of anemia or decreased hemoglobin levels.

Drug Interactions

Caution should be exercised when the following drugs are administered concomitantly with carbidopa, levodopa and entacapone tablets.

Anti-hypertensive agents: Symptomatic postural hypotension has occurred when carbidopa-levodopa was added to the treatment of patients receiving antihypertensive drugs. Therefore, when therapy with carbidopa, levodopa and entacapone tablets is started, dosage adjustment of the antihypertensive drug may be required.

MAO inhibitors: For patients receiving nonselective MAO inhibitors, see CONTRAINDICATIONS. Concomitant therapy with selegiline and carbidopa-levodopa may be associated with severe orthostatic hypotension not attributable to carbidopa-levodopa alone.

Tricyclic antidepressants: There have been rare reports of adverse reactions, including hypertension and dyskinesia, resulting from the concomitant use of tricyclic antidepressants and carbidopa-levodopa.

Dopamine D2 receptor antagonists (e.g., phenothiazines, butyrophenones, risperidone) and isoniazid: Dopamine D2 receptor antagonists (e.g., phenothiazines, butyrophenones, risperidone) and isoniazid may reduce the therapeutic effects of levodopa.

Phenytoin and papaverine: The beneficial effects of levodopa in Parkinson’s disease have been reported to be reversed by phenytoin and papaverine. Patients taking these drugs with carbidopa-levodopa should be carefully observed for loss of therapeutic response.

Iron salts: Iron salts may reduce the bioavailability of levodopa, carbidopa and entacapone. The clinical relevance is unclear.

Metoclopramide: Although metoclopramide may increase the bioavailability of levodopa by increasing gastric emptying, metoclopramide may also adversely affect disease control by its dopamine receptor antagonistic properties.

Drugs known to interfere with biliary excretion, glucuronidation, and intestinal beta-glucuronidase (probenecid, cholestyramine, erythromycin, rifampicin, ampicillin and chloramphenicol): As most entacapone excretion is via the bile, caution should be exercised when drugs known to interfere with biliary excretion, glucuronidation, and intestinal beta-glucuronidase are given concurrently with entacapone. These include probenecid, cholestyramine, and some antibiotics (e.g., erythromycin, rifampicin, ampicillin and chloramphenicol).

Pyridoxine: Carbidopa, levodopa and entacapone tablets can be given to patients receiving supplemental pyridoxine. Oral coadministration of 10 mg to 25 mg of pyridoxine hydrochloride (vitamin B6) with levodopa may reverse the effects of levodopa by increasing the rate of aromatic amino acid decarboxylation. Carbidopa inhibits this action of pyridoxine; therefore, carbidopa, levodopa and entacapone tablets can be given to patients receiving supplemental pyridoxine.

Effect of levodopa and carbidopa in carbidopa, levodopa and entacapone tablets on the metabolism of other drugs: Inhibition or induction effect of levodopa and carbidopa has not been investigated.

Effect of entacapone in carbidopa, levodopa and entacapone tablets on the metabolism of other drugs: Entacapone is unlikely to inhibit the metabolism of other drugs that are metabolized by major P450s including CYP1A2, CYP2A6, CYP2C9, CYP2C19, CYP2D6, CYP2E1 and CYP3A. In vitro studies of human CYP enzymes showed that entacapone inhibited the CYP enzymes 1A2, 2A6, 2C9, 2C19, 2D6, 2E1 and 3A only at very high concentrations (IC50 from 200 microM to over 1,000 microM; an oral 200 mg dose achieves a highest level of approximately 5 microM in people); these enzymes would therefore not be expected to be inhibited in clinical use. However, no information is available regarding the induction effect from entacapone.

Drugs that are highly protein bound (such as warfarin, salicylic acid, phenylbutazone, and diazepam):

Levodopa

Levodopa is bound to plasma protein only to a minor extent (about 10% to 30%).

Carbidopa

Carbidopa is approximately 36% bound to plasma protein.

Entacapone

Entacapone is highly protein bound (98%). In vitro studies have shown no binding displacement between entacapone and other highly bound drugs, such as warfarin, salicylic acid, phenylbutazone, and diazepam.

Hormone Levels

Of the ingredients in carbidopa, levodopa and entacapone tablets, levodopa is known to depress prolactin secretion and increase growth hormone levels.

Carcinogenesis

In a two-year bioassay of carbidopa-levodopa, no evidence of carcinogenicity was found in rats receiving doses of approximately two times the maximum daily human dose of carbidopa and four times the maximum daily human dose of levodopa.

Two-year carcinogenicity studies of entacapone were conducted in mice and rats. Rats were treated once daily by oral gavage with entacapone doses of 20 mg/kg, 90 mg/kg, or 400 mg/kg. An increased incidence of renal tubular adenomas and carcinomas was found in male rats treated with the highest dose of entacapone. Plasma exposures (AUC) associated with this dose were approximately 20 times higher than estimated plasma exposures of humans receiving the maximum recommended daily dose of entacapone (MRDD = 1,600 mg). Mice were treated once daily by oral gavage with doses of 20 mg/kg, 100 mg/kg or 600 mg/kg of entacapone (0.05, 0.3, and two times the MRDD for humans on a mg/m^2 basis). Because of a high incidence of premature mortality in mice receiving the highest dose of entacapone, the mouse study is not an adequate assessment of carcinogenicity. Although no treatment related tumors were observed in animals receiving the lower doses, the carcinogenic potential of entacapone has not been fully evaluated. The carcinogenic potential of entacapone administered in combination with carbidopa-levodopa has not been evaluated.

Mutagenesis

Carbidopa was positive in the Ames test in the presence and absence of metabolic activation, was mutagenic in the in vitro mouse lymphoma/thymidine kinase assay in the absence of metabolic activation, and was negative in the in vivo mouse micronucleus test.

Entacapone was mutagenic and clastogenic in the in vitro mouse lymphoma/thymidine kinase assay in the presence and absence of metabolic activation, and was clastogenic in cultured human lymphocytes in the presence of metabolic activation. Entacapone, either alone or in combination with carbidopalevodopa, was not clastogenic in the in vivo mouse micronucleus test or mutagenic in the bacterial reverse mutation assay (Ames test).

Impairment of Fertility

In reproduction studies with carbidopa-levodopa, no effects on fertility were found in rats receiving doses of approximately two times the maximum daily human dose of carbidopa and four times the maximum daily human dose of levodopa.

Entacapone did not impair fertility or general reproductive performance in rats treated with up to 700 mg/kg/day (plasma AUCs 28 times those in humans receiving the MRDD). Delayed mating, but no fertility impairment, was evident in female rats treated with 700 mg/kg/day of entacapone.

Pregnancy

Pregnancy Category C

Carbidopa-levodopa caused both visceral and skeletal malformations in rabbits at all doses and ratios of carbidopa-levodopa tested, which ranged from 10 times/5 times the maximum recommended human dose of carbidopa-levodopa to 20 times/10 times the maximum recommended human dose of carbidopa-levodopa. There was a decrease in the number of live pups delivered by rats receiving approximately two times the maximum recommended human dose of carbidopa and approximately five times the maximum recommended human dose of levodopa during organogenesis. No teratogenic effects were observed in mice receiving up to 20 times the maximum recommended human dose of carbidopa-levodopa.

It has been reported from individual cases that levodopa crosses the human placental barrier, enters the fetus, and is metabolized. Carbidopa concentrations in fetal tissue appeared to be minimal.

In embryo-fetal development studies, entacapone was administered to pregnant animals throughout organogenesis at doses of up to 1,000 mg/kg/day in rats and 300 mg/kg/day in rabbits. Increased incidences of fetal variations were evident in litters from rats treated with the highest dose, in the absence of overt signs of maternal toxicity. The maternal plasma drug exposure (AUC) associated with this dose was approximately 34 times the estimated plasma exposure in humans receiving the maximum recommended daily dose (MRDD) of 1,600 mg. Increased frequencies of abortions and late/total resorptions and decreased fetal weights were observed in the litters of rabbits treated with maternotoxic doses of 100 mg/kg/day (plasma AUCs 0.4 times those in humans receiving the MRDD) or greater. There was no evidence of teratogenicity in these studies.

However, when entacapone was administered to female rats prior to mating and during early gestation, an increased incidence of fetal eye anomalies (macrophthalmia, microphthalmia, anophthalmia) was observed in the litters of dams treated with doses of 160 mg/kg/day (plasma AUCs seven times those in humans receiving the MRDD) or greater, in the absence of maternotoxicity. Administration of up to 700 mg/kg/day (plasma AUCs 28 times those in humans receiving the MRDD) to female rats during the latter part of gestation and throughout lactation, produced no evidence of developmental impairment in the offspring.

There is no experience from clinical studies regarding the use of carbidopa, levodopa and entacapone tablets in pregnant women. Therefore, carbidopa, levodopa and entacapone tablets should be used during pregnancy only if the potential benefit justifies the potential risk to the fetus.

Nursing Women

In animal studies, carbidopa and entacapone were excreted into maternal rat milk. It is not known whether entacapone or carbidopa-levodopa are excreted in human milk. Because many drugs are excreted in human milk, caution should be exercised when carbidopa, levodopa and entacapone tablets are administered to a nursing woman.

Pediatric Use

Safety and effectiveness in pediatric patients have not been established.

ADVERSE REACTIONS

Carbidopa-levodopa

The most common adverse reactions reported with carbidopa-levodopa have included dyskinesias, such as choreiform, dystonic, and other involuntary movements and nausea.

The following other adverse reactions have been reported with carbidopa-levodopa:

Body as a Whole: Chest pain, asthenia.

Cardiovascular: Cardiac irregularities, hypotension, orthostatic effects including orthostatic hypotension, hypertension, syncope, phlebitis, palpitation.

Gastrointestinal: Dark saliva, gastrointestinal bleeding, development of duodenal ulcer, anorexia, vomiting, diarrhea, constipation, dyspepsia, dry mouth, taste alterations.

Hematologic: Agranulocytosis, hemolytic and non-hemolytic anemia, thrombocytopenia, leukopenia.

Hypersensitivity: Angioedema, urticaria, pruritus, Henoch-Schonlein purpura, bullous lesions (including pemphigus-like reactions).

Musculoskeletal: Back pain, shoulder pain, muscle cramps.

Nervous System/Psychiatric: Psychotic episodes including delusions, hallucinations, and paranoid ideation, neuroleptic malignant syndrome (see WARNINGS), bradykinetic episodes ("on-off" phenomenon), confusion, agitation, dizziness, somnolence, dream abnormalities including nightmares, insomnia, paresthesia, headache, depression with or without development of suicidal tendencies, dementia, increased libido. Convulsions also have occurred; however, a causal relationship with carbidopa-levodopa has not been established.

Respiratory: Dyspnea, upper respiratory infection.

Skin: Rash, increased sweating, alopecia, dark sweat.

Urogenital: Urinary tract infection, urinary frequency, dark urine.

Laboratory Tests: Decreased hemoglobin and hematocrit; abnormalities in alkaline phosphatase, SGOT (AST), SGPT (ALT), lactic dehydrogenase, bilirubin, blood urea nitrogen (BUN), Coombs’ test; elevated serum glucose; white blood cells, bacteria, and blood in the urine.

Other adverse reactions that have been reported with levodopa alone and with various carbidopa-levodopa formulations, and may occur with carbidopa, levodopa and entacapone tablets are:

Body as a Whole: Abdominal pain and distress, fatigue.

Cardiovascular: Myocardial infarction.

Gastrointestinal: Gastrointestinal pain, dysphagia, sialorrhea, flatulence, bruxism, burning sensation of the tongue, heartburn, hiccups.

Metabolic: Edema, weight gain, weight loss.

Musculoskeletal: Leg pain.

Nervous System/Psychiatric: Ataxia, extrapyramidal disorder, failing, anxiety, gait abnormalities, nervousness, decreased mental acuity, memory impairment, disorientation, euphoria, blepharospasm (which may be taken as an early sign of excess dosage; consideration of dosage reduction may be made at this time), trismus, increased tremor, numbness, muscle twitching, activation of latent Horner’s syndrome, peripheral neuropathy.

Respiratory: Pharyngeal pain, cough.

Skin: Malignant melanoma (see also CONTRAINDICATIONS), flushing.

Special Senses: Oculogyric crisis, diplopia, blurred vision, dilated pupils.

Urogenital: Urinary retention, urinary incontinence, priapism.

Miscellaneous: Bizarre breathing patterns, faintness, hoarseness, malaise, hot flashes, sense of stimulation.

Laboratory Tests: Decreased white blood cell count and serum potassium; increased serum creatinine and uric acid; protein and glucose in urine.

Entacapone

The most commonly observed adverse events (greater than 5%) in the double-blind, placebo-controlled trials of entacapone (N=1,003) associated with the use of entacapone alone and not seen at an equivalent frequency among the placebo-treated patients were: dyskinesia/hyperkinesia, nausea, urine discoloration, diarrhea, and abdominal pain.

Approximately 14% of the 603 patients given entacapone in the double-blind, placebo-controlled trials discontinued treatment due to adverse events compared to 9% of the 400 patients who received placebo. The most frequent causes of discontinuation in decreasing order are: psychiatric reasons (2% vs. 1%), diarrhea (2% vs. 0%), dyskinesia/hyperkinesia (2% vs. 1%), nausea (2% vs. 1%), abdominal pain (1% vs. 0%), and aggravation of Parkinson’s disease symptoms (1% vs. 1%).

Adverse Event Incidence in Controlled Clinical Studies of Entacapone

Table 5 lists treatment emergent adverse events that occurred in at least 1% of patients treated with entacapone participating in the double-blind, placebo-controlled studies and that were numerically more common in the entacapone group, compared to placebo. In these studies, either entacapone or placebo was added to carbidopa-levodopa (or benserazide-levodopa).

Table 5 Summary of Patients With Adverse Events After Start of Trial Drug Administration At Least 1% in Entacapone Group and Greater than Placebo
SYSTEM ORGAN CLASS Preferred Term | Entacapone (n = 603) % of patients | Placebo (n = 400) % of patients
SKIN AND APPENDAGES DISORDERS
Sweating Increased | 2 | 1
MUSCULOSKELETAL SYSTEM DISORDERS
Back Pain | 2 | 1
CENTRAL AND PERIPHERAL NERVOUS SYSTEM DISORDERS
Dyskinesia | 25 | 15
Hyperkinesia | 10 | 5
Hypokinesia | 9 | 8
Dizziness | 8 | 6
SPECIAL SENSES, OTHER DISORDERS
Taste Perversion | 1 | 0
PSYCHIATRIC DISORDERS
Anxiety | 2 | 1
Somnolence | 2 | 0
Agitation | 1 | 0
GASTROINTESTINAL SYSTEM DISORDERS
Nausea | 14 | 8
Diarrhea | 10 | 4
Abdominal Pain | 8 | 4
Constipation | 6 | 4
Vomiting | 4 | 1
Mouth Dry | 3 | 0
Dyspepsia | 2 | 1
Flatulence | 2 | 0
Gastritis | 1 | 0
Gastrointestinal Disorders NOS | 1 | 0
RESPIRATORY SYSTEM DISORDERS
Dyspnea | 3 | 1
PLATELET, BLEEDING AND CLOTTING DISORDERS
Purpura | 2 | 1
URINARY SYSTEM DISORDERS
Urine Discoloration | 10 | 0
BODY AS A WHOLE - GENERAL DISORDERS
Back Pain | 4 | 2
Fatigue | 6 | 4
Asthenia | 2 | 1
RESISTANCE MECHANISM DISORDERS
Infection Bacterial | 1 | 0

The prescriber should be aware that these figures cannot be used to predict the incidence of adverse events in the course of usual medical practice where patient characteristics and other factors differ from those that prevailed in the clinical studies. Similarly, the cited frequencies cannot be compared with figures obtained from other clinical investigations involving different treatments, uses, and investigators. The cited figures do, however, provide the prescriber with some basis for estimating the relative contribution of drug and nondrug factors to the adverse events observed in the population studied.

Effects of Gender and Age on Adverse Reactions

No differences were noted in the rate of adverse events attributable to entacapone alone by age or gender.

DRUG ABUSE AND DEPENDENCE

Controlled substance class: Carbidopa, levodopa and entacapone tablet are not controlled substances.

Physical and psychological dependence: Carbidopa, levodopa and entacapone tablets have not been systematically studied, in animal or humans, for its potential for abuse, tolerance or physical dependence. In premarketing clinical experience, carbidopa-levodopa did not reveal any tendency for a withdrawal syndrome or any drug-seeking behavior. However, there are rare postmarketing reports of abuse and dependence of medications containing levodopa. In general, these reports consist of patients taking increasing doses of medication in order to achieve a euphoric state.

OVERDOSAGE

Management of acute overdosage with carbidopa, levodopa and entacapone tablets is the same as management of acute overdosage with levodopa and entacapone. Pyridoxine is not effective in reversing the actions of carbidopa, levodopa and entacapone.

Hospitalization is advised, and general supportive measures should be employed, along with immediate gastric lavage and repeated doses of charcoal over time. This may hasten the elimination of entacapone in particular, by decreasing its absorption/reabsorption from the GI tract. Intravenous fluids should be administered judiciously and an adequate airway maintained.

The adequacy of the respiratory, circulatory and renal systems should be carefully monitored and appropriate supportive measures employed. Electrocardiographic monitoring should be instituted and the patient carefully observed for the development of arrhythmias; if required, appropriate antiarrhythmic therapy should be given. The possibility that the patient may have taken other drugs, increasing the risk of drug interactions (especially catechol-structured drugs) should be taken into consideration. To date, no experience has been reported with dialysis; hence, its value in overdosage is not known. Hemodialysis or hemoperfusion is unlikely to reduce entacapone levels due to its high binding to plasma proteins.

There are very few cases of overdosage with levodopa reported in the published literature. Based on the limited available information, the acute symptoms of levodopa/dopa decarboxylase inhibitor overdosage can be expected to arise from dopaminergic overstimulation. Doses of a few grams may result in CNS disturbances, with an increasing likelihood of cardiovascular disturbance (e.g., hypotension, tachycardia) and more severe psychiatric problems at higher doses. An isolated report of rhabdomyolysis and another of transient renal insufficiency suggest that levodopa overdosage may give rise to systemic complications, secondary to dopaminergic overstimulation.

There have been no reported cases of either accidental or intentional overdose with entacapone tablets. However, COMT inhibition by entacapone treatment is dose-dependent. A massive overdose of entacapone may theoretically produce a 100% inhibition of the COMT enzyme in people, thereby preventing the O-methylation of endogenous and exogenous catechols.

The highest single dose of entacapone administered to humans was 800 mg, resulting in a plasma concentration of 14.1 microgram/mL. The highest daily dose given to humans was 2,400 mg, administered in one study as 400 mg six times daily with carbidopa-levopoda for 14 days in 15 Parkinson’s disease patients, and in another study as 800 mg t.i.d. for 7 days in 8 healthy volunteers. At this daily dose, the peak plasma concentrations of entacapone averaged 2.0 microgram/mL (at 45 min., compared to 1.0 microgram/mL and 1.2 microgram/mL with 200 mg entacapone at 45 min.). Abdominal pain and loose stools were the most commonly observed adverse events during this study. Daily doses as high as 2,000 mg entacapone have been administered as 200 mg 10 times daily with carbidopa-levodopa or benserazide-levodopa for at least 1 year in 10 patients, for at least 2 years in 8 patients and for at least 3 years in 7 patients. Overall, however, clinical experience with daily doses above 1,600 mg is limited.

The range of lethal plasma concentrations of entacapone based on animal data was 80 microgram/mL to 130 microgram/mL in mice. Respiratory difficulties, ataxia, hypoactivity, and convulsions were observed in mice after high oral (gavage) doses.

DOSAGE AND ADMINISTRATION

Individual tablets should not be fractionated and only one tablet should be administered at each dosing interval.

Generally speaking, carbidopa, levodopa and entacapone tablets should be used as a substitute for patients already stabilized on equivalent doses of carbidopa-levodopa and entacapone. However, some patients who have been stabilized on a given dose of carbidopa-levodopa may be treated with a combination of carbidopa, levodopa and entacapone if a decision has been made to add entacapone (see below).

The optimum daily dosage of carbidopa, levodopa and entacapone tablets must be determined by careful titration in each patient. Carbidopa, levodopa and entacapone tablets are available in six strengths, each in a 1:4 ratio of carbidopa to levodopa and combined with 200 mg of entacapone in a standard release formulation (carbidopa, levodopa and entacapone tablet, containing 12.5 mg of carbidopa, 50 mg of levodopa and 200 mg of entacapone; 18.75 mg of carbidopa, 75 mg of levodopa and 200 mg of entacapone; 25 mg of carbidopa, 100 mg of levodopa and 200 mg of entacapone; 31.25 mg of carbidopa, 125 mg of levodopa and 200 mg of entacapone; 37.5 mg of carbidopa, 150 mg of levodopa and 200 mg of entacapone; and 50 mg of carbidopa, 200 mg of levodopa and 200 mg of entacapone).

Therapy should be individualized and adjusted according to the desired therapeutic response.

Studies show that peripheral dopa decarboxylase is saturated by carbidopa at approximately 70 mg to 100 mg a day. Patients receiving less than this amount of carbidopa are more likely to experience nausea and vomiting.

Clinical experience with daily doses above 1,600 mg of entacapone is limited. It is recommended that no more than one carbidopa, levodopa and entacapone tablet be taken at each dosing administration.

Thus the maximum recommended daily dose of carbidopa, levodopa and entacapone tablets, containing 50 mg, 75 mg, 100 mg, 125 mg and 150 mg of levodopa, defined by the maximum daily dose of entacapone, is eight tablets per day. Because there is limited experience with total daily doses of carbidopa greater than 300 mg, the maximum recommended daily dose of carbidopa, levodopa and entacapone tablets containing 200 mg of levodopa is six tablets per day.

How to transfer patients taking carbidopa-levodopa preparations and entacapone tablets to carbidopa, levodopa and entacapone tablets

There is no experience in transferring patients currently treated with formulations of carbidopa-levodopa other than immediate-release carbidopa-levodopa with a 1:4 ratio (controlled-release formulations, or standard-release presentations with a 1:10 ratio of carbidopa-levodopa) and entacapone to carbidopa, levodopa and entacapone tablets.

Patients who are currently treated with an entacapone 200 mg tablet with each dose of standard-release carbidopa-levodopa, can be directly switched to the corresponding strength of carbidopa, levodopa and entacapone tablet containing the same amounts of levodopa and carbidopa. For example, patients receiving one tablet of standard-release carbidopa-levodopa 25 mg/100 mg and one tablet of entacapone 200 mg at each administration can be switched to a single carbidopa, levodopa and entacapone tablet (containing 25 mg of carbidopa, 100 mg of levodopa and 200 mg of entacapone).

How to transfer patients not currently treated with entacapone tablets from carbidopa-levodopa to carbidopa, levodopa and entacapone tablets

In patients with Parkinson’s disease who experience the signs and symptoms of end-of-dose "wearing-off" on their current standard-release carbidopa-levodopa treatment, clinical experience shows that patients with a history of moderate or severe dyskinesias or taking more than 600 mg of levodopa per day are likely to require a reduction in daily levodopa dose when entacapone is added to their treatment. Since dose adjustment of the individual components is impossible with fixed-dose products, it is recommended that patients first be titrated individually with a carbidopa-levodopa product (ratio 1:4) and an entacapone product, and then transferred to a corresponding dose of carbidopa, levodopa and entacapone tablet once the patient’s status has stabilized.

In patients who take a total daily levodopa dose up to 600 mg, and who do not have dyskinesias, an attempt can be made to transfer to the corresponding daily dose of carbidopa, levodopa and entacapone tablets. Even in these patients, a reduction of carbidopa-levodopa or entacapone may be necessary however, the provider is reminded that this may not be possible with carbidopa, levodopa and entacapone tablets. Since entacapone prolongs and enhances the effects of levodopa, therapy should be individualized and adjusted if necessary according to the desired therapeutic response.

Maintenance of Carbidopa, Levodopa and Entacapone Tablet Treatment

Therapy should be individualized and adjusted for each patient according to the desired therapeutic response.

When less levodopa is required, the total daily dosage of carbidopa-levodopa should be reduced by either decreasing the strength of carbidopa, levodopa and entacapone tablets at each administration or by decreasing the frequency of administration by extending the time between doses.

When more levodopa is required, the next higher strength of carbidopa, levodopa and entacapone tablets should be taken and/or the frequency of doses should be increased, up to a maximum of 8 times daily of carbidopa, levodopa and entacapone tablets, containing 50 mg, 75 mg, 100 mg, 125 mg, and 150 mg of levodopa, and a maximum of 6 times daily of carbidopa, levodopa and entacapone tablet, containing 200 mg of levodopa.

Addition of Other Antiparkinsonian Medications

Standard drugs for Parkinson’s disease may be used concomitantly while of carbidopa, levodopa and entacapone tablets are being administered, although dosage adjustments may be required.

Interruption of Therapy

Sporadic cases of a symptom complex resembling Neuroleptic Malignant Syndrome (NMS) have been associated with dose reductions and withdrawal of levodopa preparations. Patients should be observed carefully if abrupt reduction or discontinuation of carbidopa, levodopa and entacapone tablet is required, especially if the patient is receiving neuroleptics. (See WARNINGS.)

If general anesthesia is required, carbidopa, levodopa and entacapone tablets may be continued as long as the patient is permitted to take fluids and medication by mouth. If therapy is interrupted temporarily, the patient should be observed for symptoms resembling NMS, and the usual daily dosage may be administered as soon as the patient is able to take oral medication.

Special Populations

Patients With Impaired Hepatic Function:

Patients with hepatic impairment should be treated with caution. The AUC and Cmax of entacapone approximately doubled in patients with documented liver disease, compared to controls. However, these studies were conducted with single-dose entacapone without levodopa/dopa decarboxylase inhibitor coadministration, and therefore the effects of liver disease on the kinetics of chronically administered entacapone have not been evaluated (see CLINICAL PHARMACOLOGY, Pharmacokinetics of Entacapone).

HOW SUPPLIED

Carbidopa, levodopa and entacapone are supplied as film-coated tablets for oral administration in the following six strengths:

Carbidopa, levodopa and entacapone film-coated tablets containing 12.5 mg of carbidopa, 50 mg of levodopa and 200 mg of entacapone.

The round, bi-convex shaped tablets are brownish- or grayish- red, unscored, and embossed "W782" on one side.

HDPE bottle of 100 tablets NDC 64679-782-02

HDPE bottle of 500 tablets NDC 64679-782-03

Carbidopa, levodopa and entacapone film-coated tablets containing 18.75 mg of carbidopa, 75 mg of levodopa and 200 mg of entacapone.

The oval-shaped tablets are light brownish red, unscored and embossed with code "W783" on one side.

HDPE bottle of 100 tablets NDC 64679-783-02

HDPE bottle of 500 tablets NDC 64679-783-03

Carbidopa, levodopa and entacapone film-coated tablets containing 25 mg of carbidopa, 100 mg of levodopa and 200 mg of entacapone.

The oval-shaped tablets are brownish- or grayish-red, unscored, and embossed "W784" on one side.

HDPE bottle of 100 tablets NDC 64679-784-02

HDPE bottle of 500 tablets NDC 64679-784-03

Carbidopa, levodopa and entacapone film-coated tablets containing 31.25 mg of carbidopa, 125 mg of levodopa and 200 mg of entacapone.

The oval-shaped tablets are light brownish red, unscored and embossed with code "W785" on one side.

HDPE bottle of 100 tablets NDC 64679-785-02

HDPE bottle of 500 tablets NDC 64679-785-03

Carbidopa, levodopa and entacapone film-coated tablets containing 37.5 mg of carbidopa, 150 mg of levodopa and 200 mg of entacapone

The elongated-ellipse shaped tablets are brownish- or grayish-red, unscored, and embossed "W786" on one side.

HDPE bottle of 100 tablets NDC 64679-786-02

HDPE bottle of 500 tablets NDC 64679-786-03

Carbidopa, levodopa and entacapone film-coated tablets containing 50 mg of carbidopa, 200 mg of levodopa and 200 mg of entacapone

The oval shaped tablets are dark brownish red, unscored, and embossed "W787" on one side.

HDPE bottle of 100 tablets NDC 64679-787-02

HDPE bottle of 500 tablets NDC 64679-787-03

Store at 25°C (77°F); excursions permitted to 15°C to 30°C (59°F to 86°F).

Dispense in tight container (USP).

Manufactured by:

Orion Corporation

ORION PHARMA

Orionintie 1, FIN02200 Espoo, Finland.

Distributed by:

Wockhardt USA LLC.

20 Waterview Blvd.

Parsippany, NJ 07054

USA.

Iss.150312